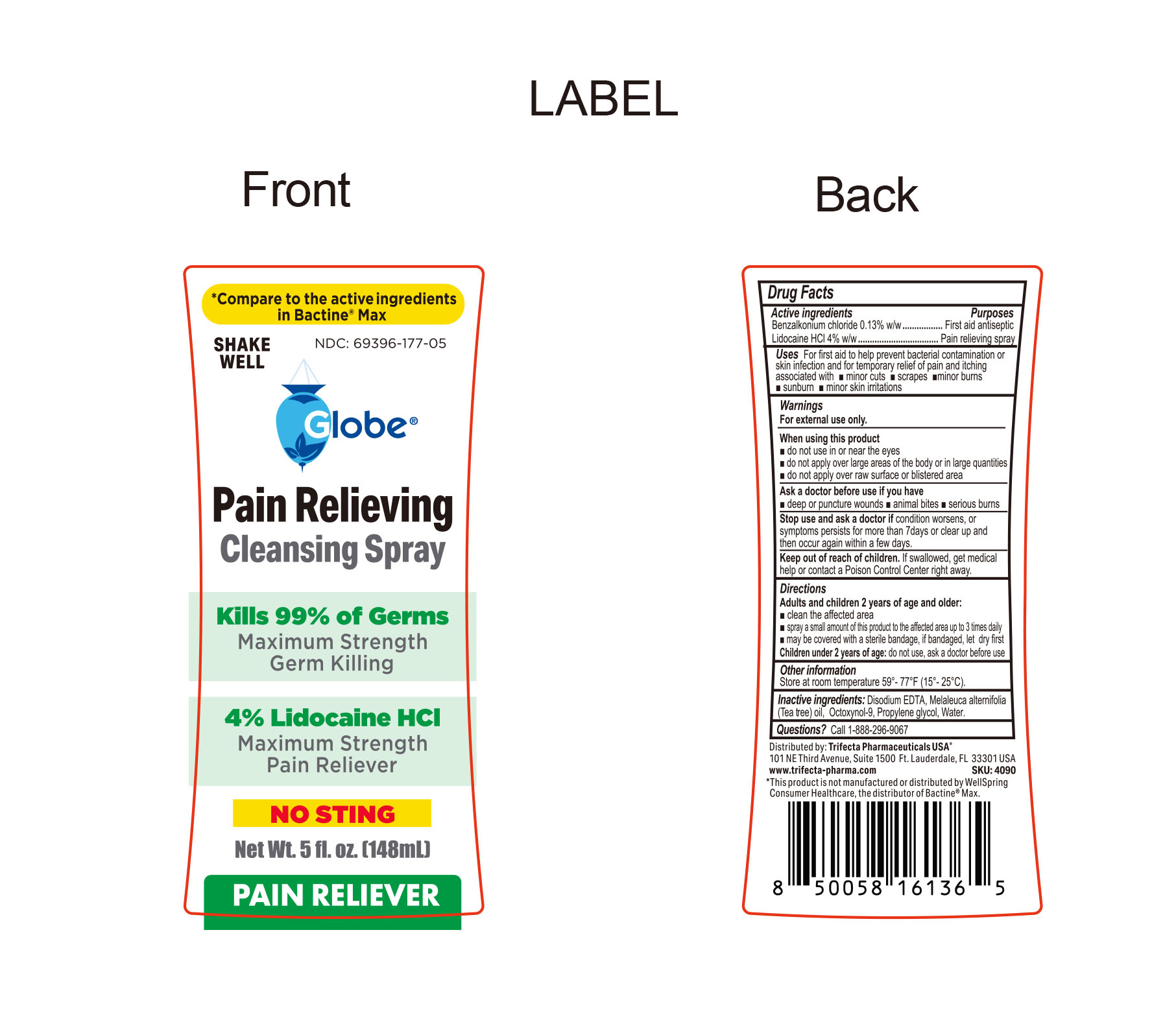 DRUG LABEL: Pain Relieving cleansing spary
NDC: 69396-177 | Form: SPRAY
Manufacturer: Trifecta Pharmaceuticals USA, LLC.
Category: otc | Type: HUMAN OTC DRUG LABEL
Date: 20260126

ACTIVE INGREDIENTS: BENZALKONIUM CHLORIDE 0.0013 g/1 mL; LIDOCAINE HYDROCHLORIDE 0.04 g/1 mL
INACTIVE INGREDIENTS: WATER; OCTOXYNOL-9; EDETATE DISODIUM; MELALEUCA ALTERNIFOLIA (TEA TREE) LEAF OIL; PROPYLENE GLYCOL

Globe Pain Relieving Cleansing Spray

Active Ingredient

Benzalkonium Chloride 0.13% w/w

Purpose

First Aid Antiseptic

Active Ingredient

Lidocaine HCI 4% w/w

Purpose

Pain Relieving Spray

Warnings

For External Use Only

Uses

For first aid to help prevent bacterial contamination skin infection and for temporary relief of pain and itching associated with

minor cuts, scrapes, minor burns, sunburn, minor skin irritations.

When Using this product

- Do not use in or near eyes
- Do not apply over large areas of the body or in large quantities
- Do not apply over raw surfact or blistered area

Ask doctor before use if you have

- Deep or puncture wounds
- Animal Bites
- Serious burns

Stop use and ask a doctor

- If the condition worsens or symptoms persists for more than 7 days or clear up and then occur again within a few days.

Keep out of the reach of children

If swallowed, get medical help or contact a Poison Control Center immediately

Directions

Adults and children 2 years of age and older:

- Clean the affected area
- Spray a small amount of this product to the affected area up to 3 times daily.
- May be covered with a sterile bandage, let dry first

Children under 2 years of age do not use, ask a doctor before use.

Other information

- Store at controlled room temperature 59º-77ºF (15º-25ºC)

Inactive Ingredients

Disodium EDTA, Melaleuca alternifolia (tea tree oil), Octoxynol-0, Propylene glycol, Water

Questions or Comments

Call 1-888-296-9067

Distributed By:

Trifecta Pharmaceuticals USA, LLC.

101 NE Third Avenue, Suite 1500

Ft. Lauderdale, FL. 33301 USA

www.trifecta-pharma.com

SKU: 4090

* This product is not manufactured or distributed by WellSpring Consumer Healthcare, the distributor of Bactine® Max.